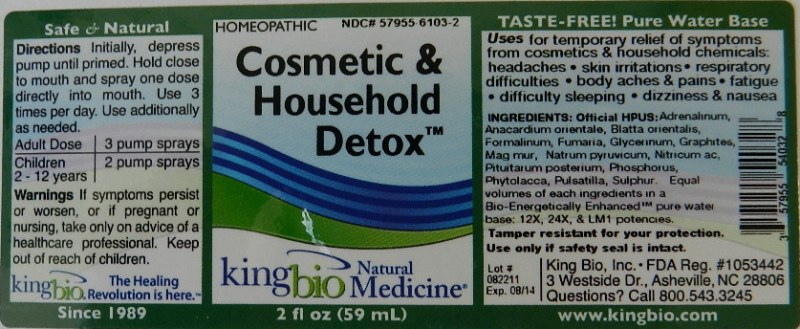 DRUG LABEL: Cosmetic and Household Detox
NDC: 57955-6103 | Form: LIQUID
Manufacturer: King Bio Inc.
Category: homeopathic | Type: HUMAN OTC DRUG LABEL
Date: 20120118

ACTIVE INGREDIENTS: EPINEPHRINE 12 [hp_X]/59 mL; SEMECARPUS ANACARDIUM JUICE 12 [hp_X]/59 mL; BLATTA ORIENTALIS 12 [hp_X]/59 mL; FORMALDEHYDE 12 [hp_X]/59 mL; FUMARIA OFFICINALIS FLOWERING TOP 12 [hp_X]/59 mL; GLYCERIN 12 [hp_X]/59 mL; GRAPHITE 12 [hp_X]/59 mL; MAGNESIUM CHLORIDE 12 [hp_X]/59 mL; SODIUM PYRUVATE 12 [hp_X]/59 mL; NITRIC ACID 12 [hp_X]/59 mL; SUS SCROFA PITUITARY GLAND 12 [hp_X]/59 mL; PHOSPHORUS 12 [hp_X]/59 mL; PHYTOLACCA AMERICANA ROOT 12 [hp_X]/59 mL; PULSATILLA VULGARIS 12 [hp_X]/59 mL; SULFUR 12 [hp_X]/59 mL
INACTIVE INGREDIENTS: WATER

Cosmetic and Household Detox

Active Ingredients

Official HPUS: Adrenalinum, Anacardium orientale, Blatta orientalis, Formalinum, Fumaria officinalis, Glycerinum, Graphites, Magnesia muriatica, Natrum pyruvicum, Nitricum acidum, Pituitarum posterium, Phosphorus, Phytolacca decandra, Pulsatilla and Sulphur.

Reference image cosmetic.jpg

Inactive Ingredient

Equal volumes of each ingredients in a Bio-Energetically Enhanced pure water base: 12X, 24X and LM1 potencies.

Reference image cosmetic.jpg

Purpose

Uses for temporary relief of symptoms from cosmetics and household chemicals:

- headaches
- skin irritations
- respiratory difficulties
- body aches and pains
- fatigue
- difficulty sleeping
- dizziness and nausea

Reference image cosmetic.jpg

Warnings

If symptoms persist or worsen, or if pregnant or nursing, take only on advice of a healthcare professional.

Other: Tamper resistant for your protection. Use only if safety seal is intact.

Reference image cosmetic.jpg

Keep out of reach of children.

Reference image cosmetic.jpg

Dosage and Administration

Directions initially, depress pump until primed. Hold close to mouth and spray one dose directly into mouth. Use 3 times per day. Use additionally as needed.

Adult Dose 3 pump sprays

Children 2-12 years 2 pump sprays

Reference image cosmetic.jpg

Indications and Usage

Uses for temporary relief of symptoms from cosmetics and household chemicals: headaches, skin irritations, respiratory difficulties, body aches and pains, fatigue, difficulty sleeping, dizziness and nausea.

Reference image cosmetic.jpg

PACKAGE LABEL

King Bio, Inc.

3 Westside Dr.

Asheville, NC 28806

Questions? Call 800.543.3245

www.kingbio.com

Safe and Natural Homeopathic